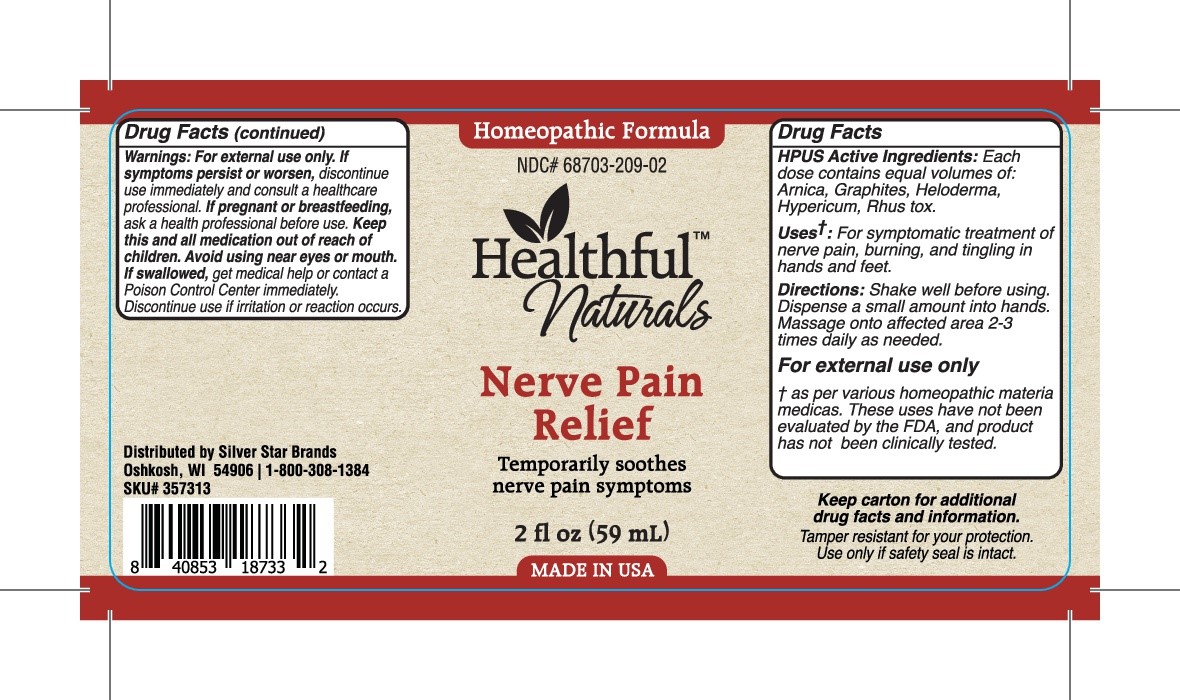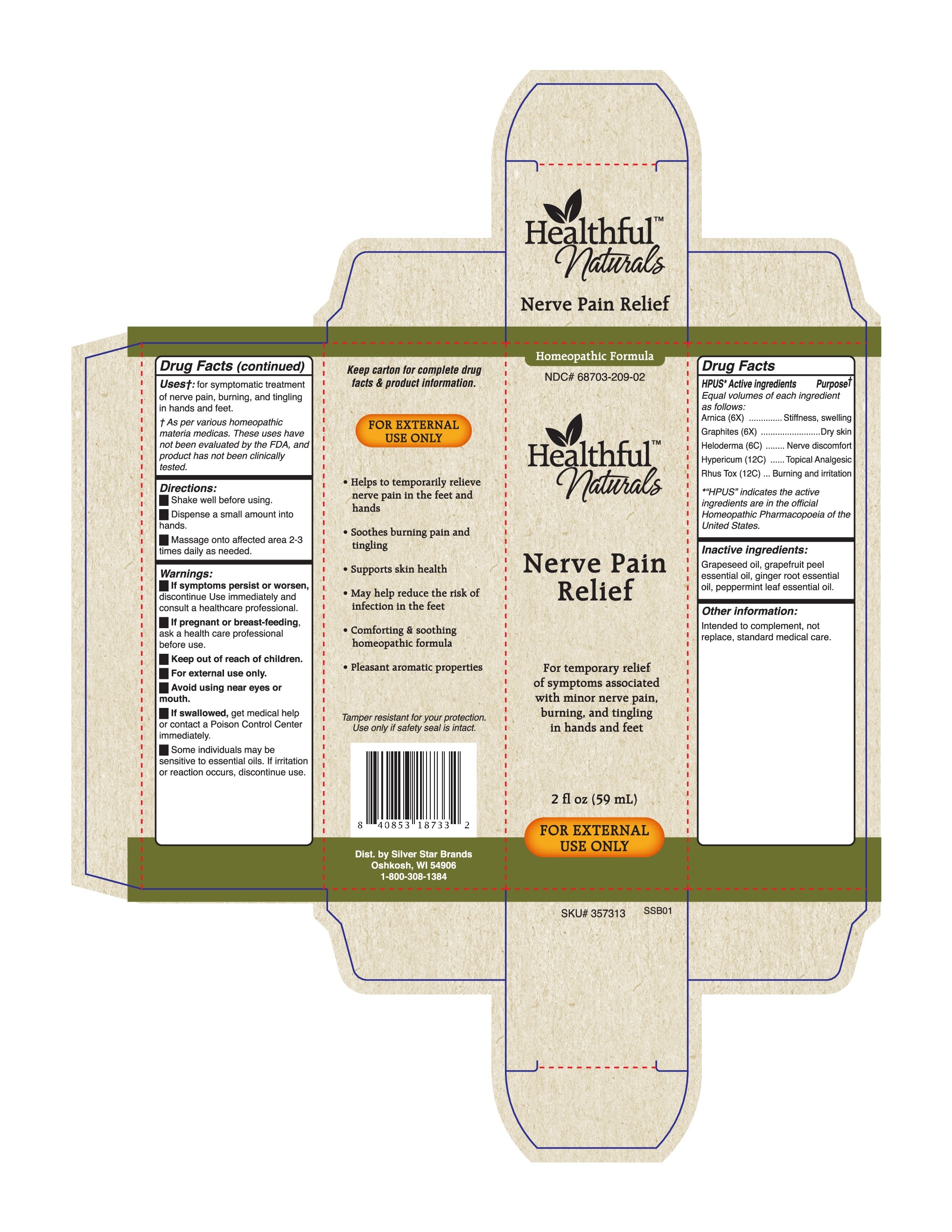 DRUG LABEL: Nerve Pain Relief
NDC: 68703-209 | Form: LIQUID
Manufacturer: Silver Star Brands
Category: homeopathic | Type: HUMAN OTC DRUG LABEL
Date: 20201202

ACTIVE INGREDIENTS: GRAPHITE 6 [hp_X]/59 mL; TOXICODENDRON RADICANS LEAF 12 [hp_C]/59 mL; ARNICA MONTANA 6 [hp_X]/59 mL; HYPERICUM PERFORATUM 12 [kp_C]/59 mL; HELODERMA HORRIDUM VENOM 6 [hp_C]/59 mL
INACTIVE INGREDIENTS: GRAPE SEED OIL; GRAPEFRUIT PEEL; ZINGIBER CASSUMUNAR ROOT OIL; EUCALYPTUS DIVES LEAFY TWIG OIL

Nerve Pain Relief Ointment

HPUS* Active ingredients: Equal volume of each ingredient as follows: Arnica (6X), Graphites (6X), Heloderma (6C), Hypericum (12C) Rhus Tox (12C).

*"HPUS" indicates the active ingredients are in the official Homeopathic Pharmacpoeia of the United States.

Uses†:

Uses†: for symptomatic treatment of nerve pain, burning, and tingling in hands and feet.

† As per various homeopathic materia medicas. These uses have not been evaluated by the FDA, and prodcut has not been clinically tested.

Warnings

Warnings:if symptoms persist or wrosen, discontinue Use immediately and consult a healthcare professional.

If pregnant or breast-feeding, ask a health care professional before use.

Keep out of reach of children.

For external use only.

Avoid using near eyes or mouth.

If swallowed, get medical help or contact a Poison Control Center immediately.

some individuals may be sensitve to essential oils, if irritation or reaction occures, discontinue use.

Directions:

Shake well before using.

dispense a small amount into hands.

Massage onto affected area 2-3 times daily as needed.

OTHER SAFETY INFORMATION

Tamper resistant for your protection. Use only if saftey seal is intact.

Inactive Ingredients

Inactive Ingredients: Grapeseed oil, grapefruit peel essential oil, ginger root essential oil, pepermint leaf essential oil.

Keep out of reach of children.

PREGNANCY OR BREAST FEEDING

If pregnant of breast-feeding, ask a health care professional before use.

PURPOSE

For temporary relief of symptoms associated with minor nerve pain, buring and tingling in hands and feet.